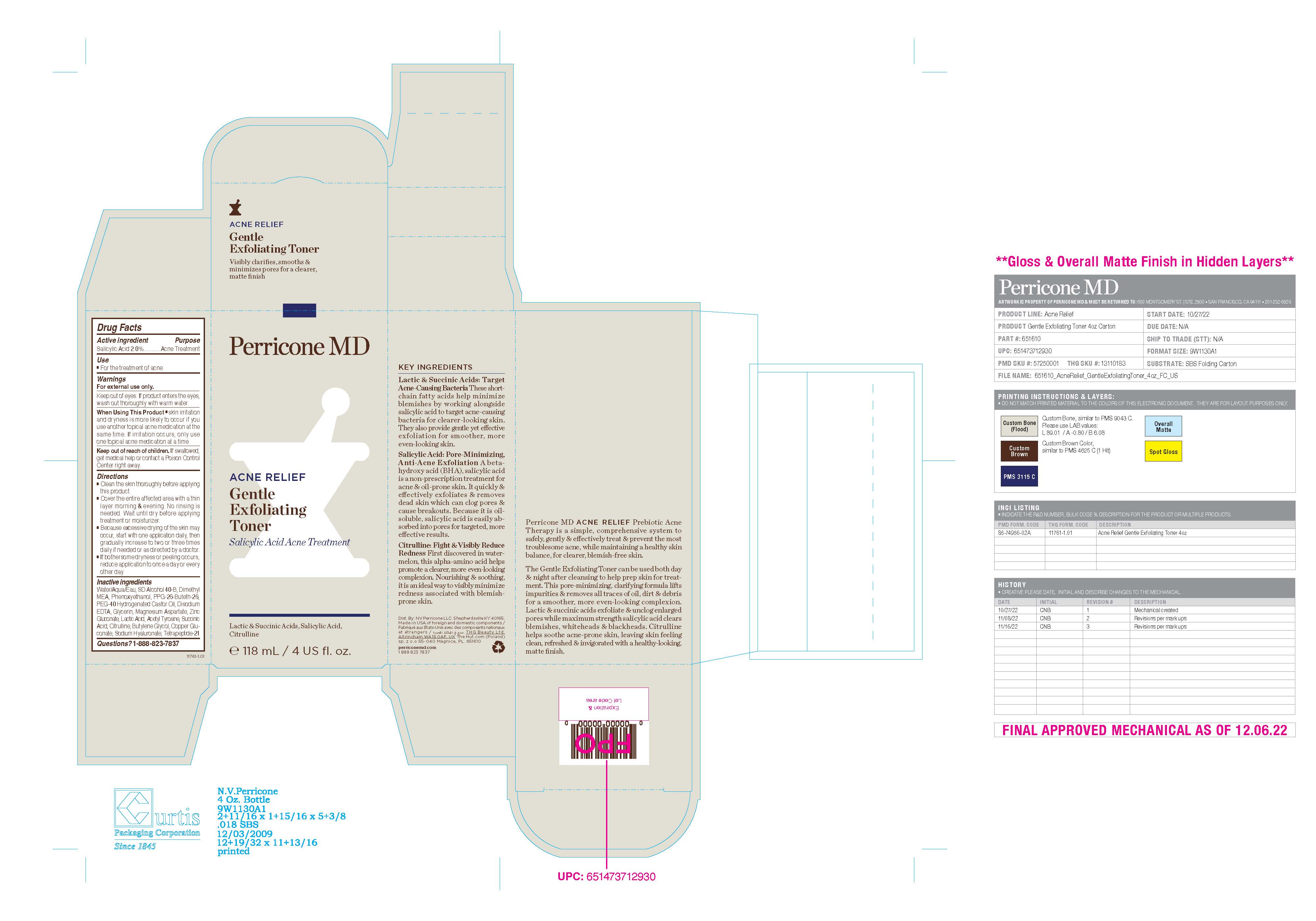 DRUG LABEL: Perricone MD Acne Relief Gentle Exfoliating Toner Salicylic Acid Acne Treatment
NDC: 84448-602 | Form: LIQUID
Manufacturer: THG Beauty USA LLC
Category: otc | Type: HUMAN OTC DRUG LABEL
Date: 20251028

ACTIVE INGREDIENTS: SALICYLIC ACID 2 g/100 mL
INACTIVE INGREDIENTS: PHENOXYETHANOL; LACTIC ACID; TETRAPEPTIDE-21; BUTYLENE GLYCOL; PPG-26-BUTETH-26; DEANOL; EDETATE DISODIUM; CITRULLINE; ZINC GLUCONATE; MAGNESIUM ASPARTATE; HYALURONATE SODIUM; WATER; SUCCINIC ACID; COPPER GLUCONATE; ACETYL L-TYROSINE; ALCOHOL; POLYOXYL 40 HYDROGENATED CASTOR OIL; GLYCERIN

ACTIVE INGREDIENT

Salicylic Acid 2.0%

PURPOSE

Acne Treatment

INDICATIONS AND USAGE

For the treatment of acne.

WARNINGS

For external use only.

Keep out of eyes. If product enters the eyes, wash out thoroughly with warm water.

When Using This Product ■ skin irritation and dryness is more likely to occur if you use another topical acne medication at the same time. If irritation occurs, only use one topical acne medication at a time

Keep out of reach of children. If swallowed, get medical help or contact a Poison Control Center right away.

DOSAGE AND ADMINISTRATION

■ Clean the skin thoroughly before applying this product. ■ Cover the entire affected area with a thin layer morning & evening. No rinsing is needed. Wait until dry before applying treatment or moisturizer. ■ Because excessive drying of the skin may occur, start with one application daily, then gradually increase to two or three times daily if needed or as directed by a doctor. ■ If bothersome dryness or peeling occurs, reduce application to once a day or every other day.

INACTIVE INGREDIENT

Water/Aqua/Eau, SD Alcohol 40-B, Dimethyl MEA, Phenoxyethanol, PPG-26-Buteth-26, PEG-40 Hydrogenated Castor Oil, Disodium EDTA, Glycerin, Magnesium Aspartate, Zinc Gluconate, Lactic Acid, Acetyl Tyrosine, Succinic Acid, Citrulline, Butylene Glycol, Copper Gluconate, Sodium Hyaluronate, Tetrapeptide-21

QUESTIONS

1-888-823-7837